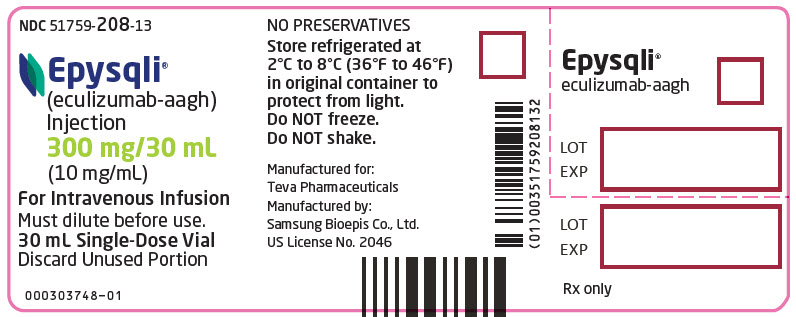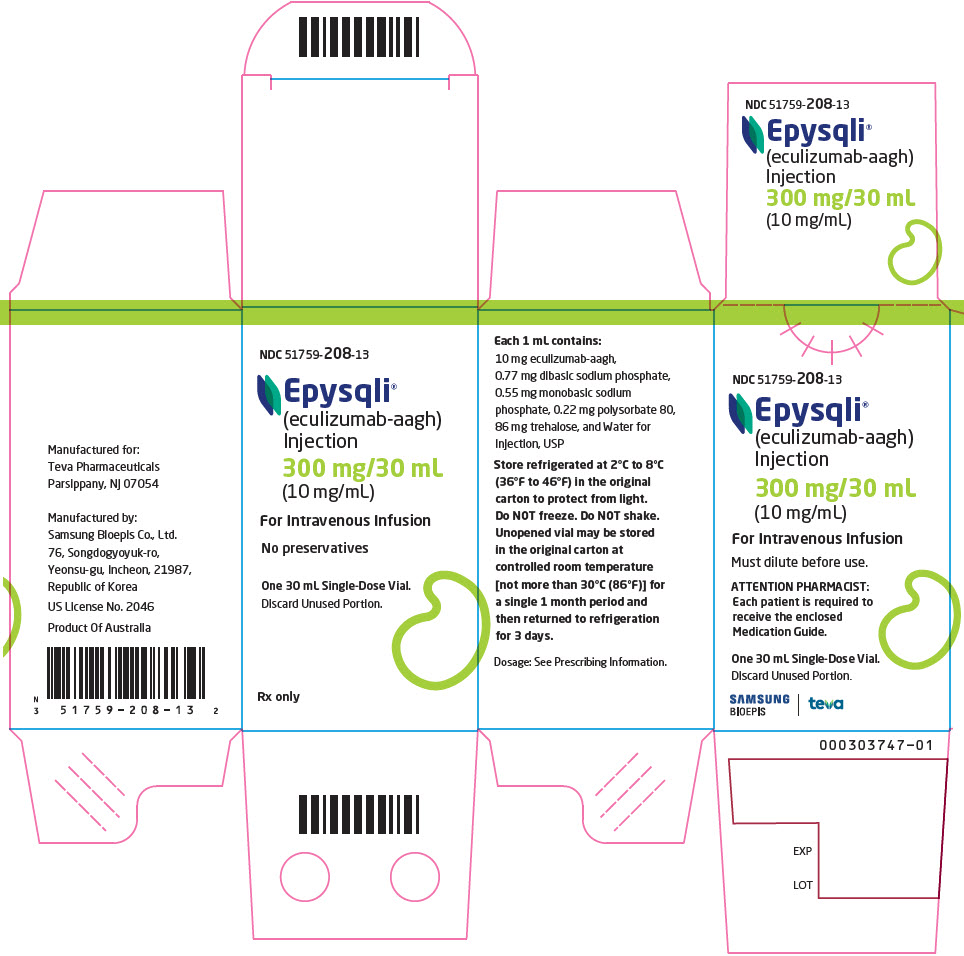 DRUG LABEL: EPYSQLI
NDC: 51759-208 | Form: INJECTION, SOLUTION
Manufacturer: Teva Pharmaceuticals USA, Inc.
Category: prescription | Type: HUMAN PRESCRIPTION DRUG LABEL
Date: 20251209

ACTIVE INGREDIENTS: Eculizumab 300 mg/30 mL
INACTIVE INGREDIENTS: polysorbate 80; sodium phosphate, dibasic, heptahydrate; sodium phosphate, monobasic, monohydrate; trehalose dihydrate; Water

HIGHLIGHTS OF PRESCRIBING INFORMATION

These highlights do not include all the information needed to use EPYSQLI safely and effectively. See full prescribing information for EPYSQLI.
EPYSQLI® (eculizumab-aagh) injection, for intravenous use
Initial U.S. Approval: 2024
EPYSQLI (eculizumab-aagh) is biosimilar [Biosimilar means that the biological product is approved based on data demonstrating that it is highly similar to an FDA approved biological product, known as a reference product, and that there are no clinically meaningful differences between the biosimilar product and the reference product. Biosimilarity of EPYSQLI has been demonstrated for the condition(s) of use (e.g., indication(s), dosing regimen(s)), strength(s), dosage form(s), and route(s) of administration described in its Full Prescribing Information.] to SOLIRIS (eculizumab).

WARNING: SERIOUS MENINGOCOCCAL INFECTIONS

See full prescribing information for complete boxed warning.

Eculizumab products increase the risk of serious and life-threatening infections caused by Neisseria meningitidis.

- Complete or update meningococcal vaccination at least 2 weeks prior to the first dose of EPYSQLI, unless the risks of delaying EPYSQLI outweigh the risk of developing a serious infection. Comply with the most current Advisory Committee on Immunization Practices (ACIP) recommendations for meningococcal vaccination in patients receiving a complement inhibitor. (5.1)
- Patients receiving eculizumab products are at increased risk for invasive disease caused by N. meningitidis, even if they develop antibodies following vaccination. Monitor patients for early signs and symptoms of meningococcal infections, and evaluate immediately if infection is suspected. (5.1)

EPYSQLI is available only through a restricted program called the EPYSQLI REMS. (5.2)

RECENT MAJOR CHANGES

Indications and Usage (1.3) | 01/2025
Dosage and Administration (2.3, 2.4, 2.5) | 11/2025

1 INDICATIONS AND USAGE

EPYSQLI is a complement inhibitor indicated for:

- the treatment of patients with paroxysmal nocturnal hemoglobinuria (PNH) to reduce hemolysis. (1.1)
- the treatment of patients with atypical hemolytic uremic syndrome (aHUS) to inhibit complement-mediated thrombotic microangiopathy. (1.2)
  Limitation of Use
  EPYSQLI is not indicated for the treatment of patients with Shiga toxin E. coli related hemolytic uremic syndrome (STEC-HUS).
- the treatment of generalized myasthenia gravis (gMG) in adult patients who are anti-acetylcholine receptor (AchR) antibody positive. (1.3)

2 DOSAGE AND ADMINISTRATION

For intravenous infusion only; recommended dosage for:

- PNH: (2.2)
- aHUS and gMG in adults: (2.3)
- aHUS in pediatric patients: (2.4)

3 DOSAGE FORMS AND STRENGTHS

Injection: 300 mg/30 mL (10 mg/mL) in a single-dose vial. (3)

4 CONTRAINDICATIONS

EPYSQLI is contraindicated for initiation in patients with unresolved serious Neisseria meningitidis infection. (4)

5 WARNINGS AND PRECAUTIONS

- Use caution when administering EPYSQLI to patients with any other systemic infection. (5.3)
- Infusion-Related Reactions: Monitor patients during infusion, interrupt for reactions, and institute appropriate supportive measures. (5.6)

6 ADVERSE REACTIONS

The most frequently reported adverse reactions in the PNH randomized trial (≥10% overall and greater than placebo) are: headache, nasopharyngitis, back pain, and nausea. (6.1)

The most frequently reported adverse reactions in aHUS single arm prospective trials (≥20%) are: headache, diarrhea, hypertension, upper respiratory infection, abdominal pain, vomiting, nasopharyngitis, anemia, cough, peripheral edema, nausea, urinary tract infections, pyrexia. (6.1)

The most frequently reported adverse reaction in the gMG placebo-controlled clinical trial (≥10%) in adult patients is musculoskeletal pain. (6.1)

To report SUSPECTED ADVERSE REACTIONS, contact Teva Pharmaceuticals at 1-888-483-8279 or FDA at 1-800-FDA-1088 or www.fda.gov/medwatch.

FULL PRESCRIBING INFORMATION

WARNING: SERIOUS MENINGOCOCCAL INFECTIONS

Eculizumab products, complement inhibitors, increase the risk of serious infections caused by Neisseria meningitidis [see Warnings and Precautions (5.1)]. Life-threatening and fatal meningococcal infections have occurred in patients treated with complement inhibitors. These infections may become rapidly life-threatening or fatal if not recognized and treated early.

- Complete or update vaccination for meningococcal bacteria (for serogroups A, C, W, Y, and B) at least 2 weeks prior to the first dose of EPYSQLI, unless the risks of delaying therapy with EPYSQLI outweigh the risk of developing a serious infection. Comply with the most current Advisory Committee on Immunization Practices (ACIP) recommendations for vaccinations against meningococcal bacteria in patients receiving a complement inhibitor. See Warnings and Precautions (5.1) for additional guidance on the management of the risk of serious infections caused by meningococcal bacteria.
- Patients receiving eculizumab products are at increased risk for invasive disease caused by Neisseria meningitidis, even if they develop antibodies following vaccination. Monitor patients for early signs and symptoms of serious meningococcal infections and evaluate immediately if infection is suspected.

Because of the risk of serious meningococcal infections, EPYSQLI is available only through a restricted program under a Risk Evaluation and Mitigation Strategy (REMS) called EPYSQLI REMS [see Warnings and Precautions (5.2)].

1 INDICATIONS AND USAGE

1.1 Paroxysmal Nocturnal Hemoglobinuria (PNH)

EPYSQLI is indicated for the treatment of patients with paroxysmal nocturnal hemoglobinuria (PNH) to reduce hemolysis.

1.2 Atypical Hemolytic Uremic Syndrome (aHUS)

EPYSQLI is indicated for the treatment of patients with atypical hemolytic uremic syndrome (aHUS) to inhibit complement-mediated thrombotic microangiopathy.

Limitation of Use

EPYSQLI is not indicated for the treatment of patients with Shiga toxin E. coli related hemolytic uremic syndrome (STEC-HUS).

1.3 Generalized Myasthenia Gravis (gMG)

EPYSQLI is indicated for the treatment of generalized myasthenia gravis (gMG) in adult patients who are anti-acetylcholine receptor (AChR) antibody positive.

2 DOSAGE AND ADMINISTRATION

2.1 Recommended Vaccination and Prophylaxis for Meningococcal Infection

Vaccinate patients against meningococcal infection (serogroups A, C, W, Y, and B) according to current ACIP recommendations at least 2 weeks prior to initiation of EPYSQLI [see Warnings and Precautions (5.1)].

If urgent EPYSQLI therapy is indicated in a patient who is not up to date with meningococcal vaccines according to ACIP recommendations, provide the patient with antibacterial drug prophylaxis and administer these vaccines as soon as possible.

Healthcare providers who prescribe EPYSQLI must enroll in the EPYSQLI REMS [see Warnings and Precautions (5.2)].

2.2 Recommended Dosage for Adults – PNH

The recommended dosage of EPYSQLI for the treatment of PNH in patients 18 years of age and older is administered as an intravenous infusion [see Dosage and Administration (2.7)] as follows:

- 600 mg weekly for the first 4 weeks, followed by
- 900 mg for the fifth dose 1 week later, then
- 900 mg every 2 weeks thereafter.

Administer EPYSQLI at the recommended dosage regimen time points, or within two days of these time points [see Warnings and Precautions (5.4)].

2.3 Recommended Dosage for Adults – aHUS and gMG

The recommended dosage of EPYSQLI for the treatment of aHUS and gMG in patients 18 years of age and older is administered as an intravenous infusion [see Dosage and Administration (2.7)] as follows:

- 900 mg weekly for the first 4 weeks, followed by
- 1,200 mg for the fifth dose 1 week later, then
- 1,200 mg every 2 weeks thereafter.

2.4 Recommended Dosage for Pediatric Patients – aHUS

The recommended dosage of EPYSQLI for the treatment of aHUS in pediatric patients less than 18 years of age is administered as an intravenous infusion based upon body weight, according to the following schedule (Table 1):

Table 1: Dosing Recommendations in Pediatric Patients Less Than 18 Years of Age with aHUS
Patient Body Weight | Induction | Maintenance
40 kg and over | 900 mg weekly for the first 4 weeks | 1,200 mg at week 5; then 1,200 mg every 2 weeks
30 kg to less than 40 kg | 600 mg weekly for the first 2 weeks | 900 mg at week 3; then 900 mg every 2 weeks
20 kg to less than 30 kg | 600 mg weekly for the first 2 weeks | 600 mg at week 3; then 600 mg every 2 weeks
10 kg to less than 20 kg | 600 mg single dose at Week 1 | 300 mg at week 2; then 300 mg every 2 weeks
5 kg to less than 10 kg | 300 mg single dose at Week 1 | 300 mg at week 2; then 300 mg every 3 weeks

Administer EPYSQLI at the recommended dosage regimen time points, or within two days of these time points.

2.5 Dose Adjustment in Case of Plasmapheresis, Plasma Exchange, Fresh Frozen Plasma Infusion or IVIg

For adult and pediatric patients with aHUS, and adult patients with gMG, supplemental dosing of EPYSQLI is required in the setting of concomitant plasmapheresis or plasma exchange, or fresh frozen plasma infusion (PE/PI) (Table 2).

Table 2: Supplemental Dose of EPYSQLI after Plasmapheresis/PE/PI
Type of Plasma Intervention | Most Recent EPYSQLI Dose | Supplemental EPYSQLI Dose with Each Plasma Intervention | Timing of Supplemental EPYSQLI Dose
Plasmapheresis or plasma exchange | 300 mg | 300 mg per each plasmapheresis or plasma exchange session | Within 60 minutes after each plasmapheresis or plasma exchange
Plasmapheresis or plasma exchange | ≥600 mg | 600 mg per each plasmapheresis or plasma exchange session | Within 60 minutes after each plasmapheresis or plasma exchange
Fresh frozen plasma infusion | ≥300 mg | 300 mg per infusion of fresh frozen plasma | 60 minutes prior to each infusion of fresh frozen plasma

For patients with gMG, a supplemental dose of EPYSQLI is required in the setting of concomitant use of intravenous immunoglobulin (IVIg) treatment as described in Table 3.

Table 3: Supplemental Dose of EPYSQLI with concomitant IVIg
IVIg Frequency | Most Recent EPYSQLI Dose | Supplemental EPYSQLI Dose per IVIg Cycle | Timing of Supplemental EPYSQLI Dose
Acute rescue therapy | No supplemental EPYSQLI dose needed
Equal to or more frequent than every 4 weeks | 900 mg or more | 600 mg | At the same time as scheduled EPYSQLI dose
Equal to or more frequent than every 4 weeks | 600 mg or less | 300 mg | At the same time as scheduled EPYSQLI dose
Less frequent than every 4 weeks | 900 mg or more | 600 mg | At the next scheduled EPYSQLI dose after the last IVIg cycle
Less frequent than every 4 weeks | 600 mg or less | 300 mg | At the next scheduled EPYSQLI dose after the last IVIg cycle

2.6 Preparation

Dilute EPYSQLI to a final admixture concentration of 5 mg/mL using the following steps:

- Withdraw the required amount of EPYSQLI from the vial into a sterile syringe.
- Transfer the recommended dose to an infusion bag.
- Dilute EPYSQLI to a final concentration of 5 mg/mL by adding the appropriate amount (equal volume of diluent to drug volume) of 0.9% Sodium Chloride Injection, USP; 0.45% Sodium Chloride Injection, USP; or 5% Dextrose in Water Injection, USP to the infusion bag.

The final admixed EPYSQLI 5 mg/mL infusion volume is 60 mL for 300 mg doses, 120 mL for 600 mg doses, 180 mL for 900 mg doses or 240 mL for 1,200 mg doses (Table 4).

Table 4: Preparation and Reconstitution of EPYSQLI
EPYSQLI Dose | Diluent Volume | Final Volume
300 mg | 30 mL | 60 mL
600 mg | 60 mL | 120 mL
900 mg | 90 mL | 180 mL
1,200 mg | 120 mL | 240 mL

Gently invert the infusion bag containing the diluted EPYSQLI solution to ensure thorough mixing of the product and diluent. Discard any unused portion left in a vial, as the product contains no preservatives.

Prior to administration, the admixture should be allowed to adjust to room temperature [18°C to 25°C (64°F to 77°F)]. The admixture must not be heated in a microwave or with any heat source other than ambient air temperature.

Parenteral drug products should be inspected visually for particulate matter and discoloration prior to administration, whenever solution and container permit.

2.7 Administration

Only administer as an intravenous infusion.

Do not administer as an intravenous push or bolus injection.

Administer the EPYSQLI admixture by intravenous infusion over 35 minutes in adults and 1 to 4 hours in pediatric patients via gravity feed, a syringe-type pump, or an infusion pump. Admixed solutions of EPYSQLI are stable for 24 hours refrigerated at 2°C to 8°C (36°F to 46°F) and at room temperature.

If an adverse reaction occurs during the administration of EPYSQLI, the infusion may be slowed or stopped at the discretion of the physician. If the infusion is slowed, the total infusion time should not exceed two hours in adults. Monitor the patient for at least one hour following completion of the infusion for signs or symptoms of an infusion-related reaction.

3 DOSAGE FORMS AND STRENGTHS

Injection: 300 mg/30 mL (10 mg/mL) as a clear to slightly opalescent, and colorless solution in a single-dose vial.

4 CONTRAINDICATIONS

EPYSQLI is contraindicated for initiation in patients with unresolved serious Neisseria meningitidis infection [see Warnings and Precautions (5.1)].

5 WARNINGS AND PRECAUTIONS

5.1 Serious Meningococcal Infections

Eculizumab products, complement inhibitors, increase a patient's susceptibility to serious, life-threatening, or fatal infections caused by meningococcal bacteria (septicemia and/or meningitis) in any serogroup, including non-groupable strains. Life-threatening and fatal meningococcal infections have occurred in both vaccinated and unvaccinated patients treated with complement inhibitors. . The initiation of EPYSQLI treatment is contraindicated in patients with unresolved serious Neisseria meningitidis infection.

Complete or update meningococcal vaccination (for serogroups A, C, W, Y, and B) at least 2 weeks prior to administration of the first dose of EPYSQLI, according to current ACIP recommendations for patients receiving a complement inhibitor. Revaccinate patients in accordance with ACIP recommendations, considering the duration of therapy with EPYSQLI. Note that ACIP recommends an administration schedule in patients receiving complement inhibitors that differs from the administration schedule in the vaccine prescribing information. If urgent EPYSQLI therapy is indicated in a patient who is not up to date with meningococcal vaccines according to ACIP recommendations, provide the patient with antibacterial drug prophylaxis and administer meningococcal vaccines as soon as possible. Various durations and regimens of antibacterial drug prophylaxis have been considered, but the optimal durations and drug regimens for prophylaxis and their efficacy have not been studied in unvaccinated or vaccinated patients receiving complement inhibitors, including eculizumab products. The benefits and risks of treatment with EPYSQLI, as well as the benefits and risks of antibacterial drug prophylaxis in unvaccinated or vaccinated patients, must be considered against the known risks for serious infections caused by Neisseria meningitidis.

Vaccination does not eliminate the risk of serious meningococcal infections, despite development of antibodies following vaccination.

Closely monitor patients for early signs and symptoms of meningococcal infection and evaluate patients immediately if infection is suspected. Inform patients of these signs and symptoms and instruct patients to seek immediate medical care if these signs and symptoms occur. Promptly treat known infections. Meningococcal infection may become rapidly life- threatening or fatal if not recognized and treated early. Consider interruption of EPYSQLI in patients who are undergoing treatment for serious meningococcal infection, depending on the risks of interrupting treatment in the disease being treated.

EPYSQLI is available only through a restricted program under a REMS [see Warnings and Precautions (5.2)].

5.2 EPYSQLI REMS

EPYSQLI is available only through a restricted program under a REMS called EPYSQLI REMS, because of the risk of serious meningococcal infections [see Warnings and Precautions (5.1)].

Notable requirements of the EPYSQLI REMS include the following:

- Prescribers must enroll in the REMS.
- Prescribers must counsel patients about the risk of serious meningococcal infection.
- Prescribers must provide the patients with the REMS educational materials.
- Prescribers must assess patient vaccination status for meningococcal vaccines (against serogroups A, C, W, Y and B) and vaccinate if needed according to current ACIP recommendations two weeks prior to the first dose of EPYSQLI.
- Prescribers must provide a prescription for antibacterial drug prophylaxis if treatment must be started urgently and the patient is not up to date with meningococcal vaccines according to current ACIP recommendations at least two weeks prior to the first dose of EPYSQLI.
- Healthcare settings and pharmacies that dispense EPYSQLI must be certified in the REMS and must verify prescribers are certified.
- Patients must receive counseling from the prescriber about the need to receive meningococcal vaccines per ACIP recommendations, the need to take antibiotics as directed by the prescriber, and the signs and symptoms of meningococcal infection.
- Patients must be instructed to carry the Patient Safety Card with them at all times during and for 3 months following treatment with EPYSQLI.

Further information is available at www.EPYSQLIREMS.com or 1-866-318-0342.

5.3 Other Infections

Serious infections with Neisseria species (other than Neisseria meningitidis), including disseminated gonococcal infections, have been reported.

Eculizumab products block terminal complement activation; therefore, patients may have increased susceptibility to infections, especially with encapsulated bacteria, such as infections with Neisseria meningitidis but also Streptococcus pneumoniae, Haemophilus influenzae, and to a lesser extent, Neisseria gonorrhoeae. Additionally, Aspergillus infections have occurred in immunocompromised and neutropenic patients. Children treated with eculizumab products may be at increased risk of developing serious infections due to Streptococcus pneumoniae and Haemophilus influenzae type b (Hib). Administer vaccinations for the prevention of Streptococcus pneumoniae and Haemophilus influenzae type b (Hib) infections according to ACIP recommendations. Patients receiving eculizumab products are at increased risk for infections due to these organisms, even if they develop antibodies following vaccination.

5.4 Monitoring Disease Manifestations after EPYSQLI Discontinuation

Treatment Discontinuation for PNH

Monitor patients after discontinuing EPYSQLI for at least 8 weeks to detect hemolysis.

Treatment Discontinuation for aHUS

After discontinuing EPYSQLI, monitor patients with aHUS for signs and symptoms of thrombotic microangiopathy (TMA) complications for at least 12 weeks. In aHUS clinical trials, 18 patients (5 in the prospective studies) discontinued eculizumab treatment. TMA complications occurred following a missed dose in 5 patients, and eculizumab was reinitiated in 4 of these 5 patients.

Clinical signs and symptoms of TMA include changes in mental status, seizures, angina, dyspnea, or thrombosis. In addition, the following changes in laboratory parameters may identify a TMA complication: occurrence of two, or repeated measurement of any one of the following: a decrease in platelet count by 25% or more compared to baseline or the peak platelet count during EPYSQLI treatment; an increase in serum creatinine by 25% or more compared to baseline or nadir during EPYSQLI treatment; or, an increase in serum LDH by 25% or more over baseline or nadir during EPYSQLI treatment.

If TMA complications occur after EPYSQLI discontinuation, consider reinstitution of EPYSQLI treatment, plasma therapy [plasmapheresis, plasma exchange, or fresh frozen plasma infusion (PE/PI)], or appropriate organ-specific supportive measures.

5.5 Thrombosis Prevention and Management

The effect of withdrawal of anticoagulant therapy during eculizumab products treatment has not been established. Therefore, treatment with eculizumab products should not alter anticoagulant management.

5.6 Infusion-Related Reactions

Administration of eculizumab products may result in infusion-related reactions, including anaphylaxis or other hypersensitivity reactions. In clinical trials, no patients experienced an infusion-related reaction which required discontinuation of eculizumab. Interrupt EPYSQLI infusion and institute appropriate supportive measures if signs of cardiovascular instability or respiratory compromise occur.

6 ADVERSE REACTIONS

The following serious adverse reactions are discussed in greater detail in other sections of the labeling:

- Serious Meningococcal Infections [see Warnings and Precautions (5.1)]
- Other Infections [see Warnings and Precautions (5.3)]
- Monitoring Disease Manifestations after EPYSQLI Discontinuation [see Warnings and Precautions (5.4)]
- Thrombosis Prevention and Management [see Warnings and Precautions (5.5)]
- Infusion-Related Reactions [see Warnings and Precautions (5.6)]

6.1 Clinical Trial Experience

Because clinical trials are conducted under widely varying conditions, adverse reaction rates observed in the clinical trials of a drug cannot be directly compared to rates in the clinical trials of another drug and may not reflect the rates observed in practice.

Meningococcal infections are the most important adverse reactions experienced by patients receiving eculizumab. In PNH clinical studies, two patients experienced meningococcal sepsis. Both patients had previously received a meningococcal vaccine. In clinical studies among patients without PNH, meningococcal meningitis occurred in one unvaccinated patient. Meningococcal sepsis occurred in one previously vaccinated patient enrolled in the retrospective aHUS study during the post-study follow-up period [see Warnings and Precautions (5.1)].

PNH

The data described below reflect exposure to eculizumab in 196 adult patients with PNH, age 18-85, of whom 55% were female. All had signs or symptoms of intravascular hemolysis. Eculizumab was studied in a placebo-controlled clinical study (PNH Study 1, in which 43 patients received eculizumab and 44, placebo); a single arm clinical study (PNH Study 2); and a long term extension study (E05-001). 182 patients were exposed for greater than one year. All patients received the recommended eculizumab dose regimen.

Table 4 summarizes the adverse reactions that occurred at a numerically higher rate in the eculizumab group than the placebo group and at a rate of 5% or more among patients treated with eculizumab.

Table 5: Adverse Reactions Reported in 5% or More of Eculizumab Treated Patients with PNH and Greater than Placebo in the Controlled Clinical Study
Reaction | Eculizumab | Placebo
Reaction | (N=43) | (N=44)
Reaction | N (%) | N (%)
Headache | 19 (44) | 12 (27)
Nasopharyngitis | 10 (23) | 8 (18)
Back pain | 8 (19) | 4 (9)
Nausea | 7 (16) | 5 (11)
Fatigue | 5 (12) | 1 (2)
Cough | 5 (12) | 4 (9)
Herpes simplex infections | 3 (7) | 0
Sinusitis | 3 (7) | 0
Respiratory tract infection | 3 (7) | 1 (2)
Constipation | 3 (7) | 2 (5)
Myalgia | 3 (7) | 1 (2)
Pain in extremity | 3 (7) | 1 (2)
Influenza-like illness | 2 (5) | 1 (2)

In the placebo-controlled clinical study, serious adverse reactions occurred among 4 (9%) patients receiving eculizumab and 9 (21%) patients receiving placebo. The serious reactions included infections and progression of PNH. No deaths occurred in the study and no patients receiving eculizumab experienced a thrombotic event; one thrombotic event occurred in a patient receiving placebo.

Among 193 patients with PNH treated with eculizumab in the single arm, clinical study or the follow-up study, the adverse reactions were similar to those reported in the placebo-controlled clinical study. Serious adverse reactions occurred among 16% of the patients in these studies. The most common serious adverse reactions were: viral infection (2%), headache (2%), anemia (2%), and pyrexia (2%).

aHUS

The safety of eculizumab therapy in patients with aHUS was evaluated in four prospective, single-arm studies, three in adult and adolescent patients (Studies C08-002A/B, C08-003A/B, and C10-004), one in pediatric and adolescent patients (Study C10-003), and one retrospective study (Study C09-001r).

The data described below were derived from 78 adult and adolescent patients with aHUS in Studies C08-002A/B, C08-003A/B and C10-004. All patients received the recommended dosage of eculizumab. Median exposure was 67 weeks (range: 2-145 weeks). Table 6 summarizes all adverse events reported in at least 10% of patients in Studies C08-002A/B, C08-003A/B and C10-004 combined.

Table 6: Per Patient Incidence of Adverse Events in 10% or More Adult and Adolescent Patients Enrolled in Studies C08-002A/B, C08-003A/B and C10-004 Separately and in Total
 | Number (%) of Patients
 | C08-002A/B | C08-003A/B | C10-004 | Total
 | (N=17) | (N=20) | (N=41) | (N=78)
Vascular Disorders
Hypertensiona | 10 (59) | 9 (45) | 7 (17) | 26 (33)
Hypotension | 2 (12) | 4 (20) | 7 (17) | 13 (17)
Infections and Infestations
Bronchitis | 3 (18) | 2 (10) | 4 (10) | 9 (12)
Nasopharyngitis | 3 (18) | 11 (55) | 7 (17) | 21 (27)
Gastroenteritis | 3 (18) | 4 (20) | 2 (5) | 9 (12)
Upper respiratory tract infection | 5 (29) | 8 (40) | 2 (5) | 15 (19)
Urinary tract infection | 6 (35) | 3 (15) | 8 (20) | 17 (22)
Gastrointestinal Disorders
Diarrhea | 8 (47) | 8 (40) | 12 (32) | 29 (37)
Vomiting | 8 (47) | 9 (45) | 6 (15) | 23 (30)
Nausea | 5 (29) | 8 (40) | 5 (12) | 18 (23)
Abdominal pain | 3 (18) | 6 (30) | 6 (15) | 15 (19)
Nervous System Disorders
Headache | 7 (41) | 10 (50) | 15 (37) | 32 (41)
Blood and Lymphatic System Disorders
Anemia | 6 (35) | 7 (35) | 7 (17) | 20 (26)
Leukopenia | 4 (24) | 3 (15) | 5 (12) | 12 (15)
Psychiatric Disorders
Insomnia | 4 (24) | 2 (10) | 5 (12) | 11 (14)
Renal and Urinary Disorders
Renal Impairment | 5 (29) | 3 (15) | 6 (15) | 14 (18)
Proteinuria | 2 (12) | 1 (5) | 5 (12) | 8 (10)
Respiratory, Thoracic and Mediastinal Disorders
Cough | 4 (24) | 6 (30) | 8 (20) | 18 (23)
General Disorders and Administration Site Conditions
Fatigue | 3 (18) | 4 (20) | 3 (7) | 10 (13)
Peripheral edema | 5 (29) | 4 (20) | 9 (22) | 18 (23)
Pyrexia | 4 (24) | 5 (25) | 7 (17) | 16 (21)
Asthenia | 3 (18) | 4 (20) | 6 (15) | 13 (17)
Eye Disorder | 5 (29) | 2 (10) | 8 (20) | 15 (19)
Metabolism and Nutrition Disorders
Hypokalemia | 3 (18) | 2 (10) | 4 (10) | 9 (12)
Neoplasms benign, malignant, and unspecified (including cysts and polyps) | 1 (6) | 6 (30) | 1 (20) | 8 (10)
Skin and Subcutaneous Tissue Disorders
Rash | 2 (12) | 3 (15) | 6 (15) | 11 (14)
Pruritus | 1 (6) | 3 (15) | 4 (10) | 8 (10)
Musculoskeletal and Connective Tissue Disorders
Arthralgia | 1 (6) | 2 (10) | 7 (17) | 10 (13)
Back pain | 3 (18) | 3 (15) | 2 (5) | 8 (10)
a. includes the preferred terms hypertension, accelerated hypertension, and malignant hypertension.

In Studies C08-002A/B, C08-003A/B and C10-004 combined, 60% (47/78) of patients experienced a serious adverse event (SAE). The most commonly reported SAEs were infections (24%), hypertension (5%), chronic renal failure (5%), and renal impairment (5%). Five patients discontinued eculizumab due to adverse events; three due to worsening renal function, one due to new diagnosis of Systemic Lupus Erythematosus, and one due to meningococcal meningitis.

Study C10-003 included 22 pediatric and adolescent patients, of which 18 patients were less than 12 years of age. All patients received the recommended dosage of eculizumab. Median exposure was 44 weeks (range: 1 dose-87 weeks).

Table 6 summarizes all adverse events reported in at least 10% of patients enrolled in Study C10-003.

Table 7: Per Patient Incidence of Adverse Reactions in 10% or More Patients Enrolled in Study C10-003
 | 1 month to <12 yrs (N=18) | Total (N=22)
Eye Disorders | 3 (17) | 3 (14)
Gastrointestinal Disorders
Abdominal pain | 6 (33) | 7 (32)
Diarrhea | 5 (28) | 7 (32)
Vomiting | 4 (22) | 6 (27)
Dyspepsia | 0 | 3 (14)
General Disorders and Administration Site Conditions
Pyrexia | 9 (50) | 11 (50)
Infections and Infestations
Upper respiratory tract infection | 5 (28) | 7 (32)
Nasopharyngitis | 3 (17) | 6 (27)
Rhinitis | 4 (22) | 4 (18)
Urinary Tract infection | 3 (17) | 4 (18)
Catheter site infection | 3 (17) | 3 (14)
Musculoskeletal and Connective Tissue Disorders
Muscle spasms | 2 (11) | 3 (14)
Nervous System Disorders
Headache | 3 (17) | 4 (18)
Renal and Urinary Disorders | 3 (17) | 4 (18)
Respiratory, Thoracic and Mediastinal Disorders
Cough | 7 (39) | 8 (36)
Oropharyngeal pain | 1 (6) | 3 (14)
Skin and Subcutaneous Tissue Disorders
Rash | 4 (22) | 4 (18)
Vascular Disorders
Hypertension | 4 (22) | 4 (18)

In Study C10-003, 59% (13/22) of patients experienced a serious adverse event (SAE). The most commonly reported SAEs were hypertension (9%), viral gastroenteritis (9%), pyrexia (9%), and upper respiratory infection (9%). One patient discontinued eculizumab due to an adverse event (severe agitation).

Analysis of retrospectively collected adverse event data from pediatric and adult patients enrolled in Study C09-001r (N=30) revealed a safety profile that was similar to that which was observed in the two prospective studies. Study C09-001r included 19 pediatric patients less than 18 years of age.

Overall, the safety of eculizumab in pediatric patients with aHUS enrolled in Study C09-001r appeared similar to that observed in adult patients. The most common (≥15%) adverse events occurring in pediatric patients are presented in Table 8.

Table 8: Adverse Reactions Occurring in at Least 15% of Patients Less than 18 Years of Age Enrolled in Study C09-001r
 | Number (%) of Patients
 | < 2 yrs (N=5) | 2 to < 12 yrs (N=10) | 12 to < 18 yrs (N=4) | Total (N=19)
General Disorders and Administration Site Conditions
Pyrexia | 4 (80) | 4 (40) | 1 (25) | 9 (47)
Gastrointestinal Disorders
Diarrhea | 1 (20) | 4 (40) | 1 (25) | 6 (32)
Vomiting | 2 (40) | 1 (10) | 1 (25) | 4 (21)
Infections and Infestations
Upper respiratory tract infectiona | 2 (40) | 3 (30) | 1 (25) | 6 (32)
Respiratory, Thoracic and Mediastinal Disorders
Cough | 3 (60) | 2 (20) | 0 (0) | 5 (26)
Nasal congestion | 2 (40) | 2 (20) | 0 (0) | 4 (21)
Cardiac Disorders
Tachycardia | 2 (40) | 2 (20) | 0 (0) | 4 (21)
a. includes the preferred terms upper respiratory tract infection and nasopharyngitis.

Generalized Myasthenia Gravis (gMG)

Adults

In a 26-week placebo-controlled trial evaluating the effect of eculizumab for the treatment of adult patients with gMG (Study ECU-MG-301), 62 patients received eculizumab at the recommended dosage regimen and 63 patients received placebo [see Clinical Studies (14.3)]. Patients were 19 to 79 years of age, and 66% were female. Table 9 displays the most common adverse reactions from gMG Study 1 that occurred in ≥5% of eculizumab-treated patients and at a greater frequency than on placebo.

Table 9: Adverse Reactions Reported in 5% or More of Eculizumab-Treated Patients in Study ECU-MG-301 and at a Greater Frequency than in Placebo-Treated Patients
 | Eculizumab (N=62) N (%) | Placebo (N=63) N (%)
Gastrointestinal Disorders
Abdominal pain | 5 (8) | 3 (5)
General Disorders and Administration Site Conditions
Peripheral edema | 5 (8) | 3 (5)
Pyrexia | 4 (7) | 2 (3)
Infections and Infestations
Herpes simplex virus infections Herpes simplex virus infections | 5 (8) | 1 (2)
Injury, Poisoning, and Procedural Complications
Contusion | 5 (8) | 2 (3)
Musculoskeletal and Connective Tissue Disorders
Musculoskeletal pain | 9 (15) | 5 (8)

The most common adverse reactions (≥10%) that occurred in eculizumab-treated patients in the long-term extension to Study ECU-MG-301, Study ECU-MG-302, and that are not included in Table 8 were headache (26%), nasopharyngitis (24%), diarrhea (15%), arthralgia (12%), upper respiratory tract infection (11%), and nausea (10%).

6.2 Postmarketing Experience

The following adverse reactions have been identified during post-approval use of eculizumab products. Because these reactions are reported voluntarily from a population of uncertain size, it is not always possible to reliably estimate their frequency or establish a causal relationship to eculizumab products exposure.

Adverse Reactions from Postmarketing Spontaneous Reports

- Fatal or serious infections: Neisseria gonorrhoeae, Neisseria meningitidis, Neisseria sicca/subflava, Neisseria spp unspecified.
- Cases of cholestatic or mixed pattern liver injury with increased serum liver enzymes and bilirubin levels have been reported in adult and pediatric patients with aHUS who were treated with eculizumab products. These events occurred within 3 to 27 days after starting treatment. The median time to resolution (or return to baseline) was approximately 3 weeks.

7 DRUG INTERACTIONS

7.1 Plasmapheresis, Plasma Exchange, Fresh Frozen Plasma Infusion or IVIg

Concomitant use of eculizumab products with plasma exchange (PE), plasmapheresis (PP), fresh frozen plasma infusion (PE/PI), or in patients with gMG on concomitant IVIg treatment can reduce serum eculizumab product concentrations and requires a supplemental dose of EPYSQLI [see Dosage and Administration (2.5)].

7.2 Neonatal Fc Receptor Blockers

Concomitant use of eculizumab products with neonatal Fc receptor (FcRn) blockers may lower systemic exposures and reduce effectiveness of eculizumab products. Closely monitor for reduced effectiveness of EPYSQLI.

8 USE IN SPECIFIC POPULATIONS

8.1 Pregnancy

Risk Summary

Limited data on outcomes of pregnancies that have occurred following eculizumab use in pregnant women have not identified a concern for specific adverse developmental outcomes (see Data). There are risks to the mother and fetus associated with untreated paroxysmal nocturnal hemoglobinuria (PNH) and atypical hemolytic uremic syndrome (aHUS) in pregnancy (see Clinical Considerations). Animal studies using a mouse analogue of the eculizumab molecule (murine anti-C5 antibody) showed increased rates of developmental abnormalities and an increased rate of dead and moribund offspring at doses 2-8 times the human dose (see Data).

The estimated background risk of major birth defects and miscarriage for the indicated populations is unknown. All pregnancies have a background risk of birth defect, loss, or other adverse outcomes. In the U.S. general population, the estimated background risk of major birth defect and miscarriage in clinically recognized pregnancies is 2-4% and 15-20%, respectively.

Clinical Considerations

Disease-Associated Maternal and/or Fetal/Neonatal Risk

PNH in pregnancy is associated with adverse maternal outcomes, including worsening cytopenias, thrombotic events, infections, bleeding, miscarriages and increased maternal mortality, and adverse fetal outcomes, including fetal death and premature delivery.

aHUS in pregnancy is associated with adverse maternal outcomes, including pre-eclampsia and preterm delivery, and adverse fetal/neonatal outcomes, including intrauterine growth restriction (IUGR), fetal death and low birth weight.

Data

Human Data

A pooled analysis of prospectively (50.3%) and retrospectively (49.7%) collected data in more than 300 pregnant women with live births following exposure to eculizumab have not suggested safety concerns. However, these data cannot definitively exclude any drug-associated risk during pregnancy, because of the limited sample size.

Animal Data

Animal reproduction studies were conducted in mice using doses of a murine anti-C5 antibody that approximated 2-4 times (low dose) and 4-8 times (high dose) the recommended human eculizumab dose, based on a body weight comparison. When animal exposure to the antibody occurred in the time period from before mating until early gestation, no decrease in fertility or reproductive performance was observed. When maternal exposure to the antibody occurred during organogenesis, two cases of retinal dysplasia and one case of umbilical hernia were observed among 230 offspring born to mothers exposed to the higher antibody dose; however, the exposure did not increase fetal loss or neonatal death. When maternal exposure to the antibody occurred in the time period from implantation through weaning, a higher number of male offspring became moribund or died (1/25 controls, 2/25 low dose group, 5/25 high dose group). Surviving offspring had normal development and reproductive function.

8.2 Lactation

Risk Summary

Although limited published data does not report detectable levels of eculizumab in human milk, maternal IgG is known to be present in human milk. Available information is insufficient to inform the effect of eculizumab products on the breastfed infant. There are no data on the effects of eculizumab products on milk production. The developmental and health benefits of breastfeeding should be considered along with the mother's clinical need for EPYSQLI and any potential adverse effects on the breastfed child from EPYSQLI or from the underlying maternal condition.

8.4 Pediatric Use

PNH

Safety and effectiveness of EPYSQLI for the treatment of PNH in pediatric patients have not been established.

aHUS

The safety and effectiveness of EPYSQLI for the treatment of aHUS have been established in pediatric patients. Use of EPYSQLI in pediatric patients for this indication is supported by evidence from four adequate and well-controlled clinical studies assessing the safety and effectiveness of eculizumab for the treatment of aHUS. The studies included a total of 47 pediatric patients (ages 2 months to 17 years). The safety and effectiveness of eculizumab for the treatment of aHUS appear similar in pediatric and adult patients [see Adverse Reactions (6.1), and Clinical Studies (14.2)].

A pediatric assessment for EPYSQLI demonstrates that EPYSQLI is safe and effective for pediatric patients in an indication for which Soliris (eculizumab) is approved. However, EPYSQLI is not approved for such indication due to marketing exclusivity for Soliris (eculizumab).

Vaccinations

Administer vaccinations for the prevention of infection due to Neisseria meningitidis, Streptococcus pneumoniae and Haemophilus influenzae type b (Hib) according to ACIP guidelines [see Warnings and Precautions (5.1, 5.3)].

8.5 Geriatric Use

Fifty-one patients 65 years of age or older (15 with PNH, 4 with aHUS, 26 with gMG, and 6 with another indication) were treated with eculizumab in clinical trials in the approved indications. Although there were no apparent age-related differences observed in these studies, the number of patients aged 65 and over is not sufficient to determine whether they respond differently from younger patients.

11 DESCRIPTION

Eculizumab-aagh, a complement inhibitor, is a recombinant humanized monoclonal IgG2/4κ antibody produced in a Chinese Hamster Ovary cell line expression system and purified by standard bioprocess technology .

Eculizumab-aagh contains human constant regions from human IgG2 sequences and human IgG4 sequences and murine complementarity-determining regions grafted onto the human framework light- and heavy-chain variable regions. Eculizumab-aagh is composed of two 448 amino acid heavy chains and two 214 amino acid light chains and has a molecular weight of approximately 148 kDa.

EPYSQLI (eculizumab-aagh) injection is a sterile, preservative-free, clear to slightly opalescent and colorless solution for intravenous infusion and is supplied in a 30 mL single-dose vial. Each mL contains 10 mg of eculizumab-aagh, dibasic sodium phosphate (0.77 mg), monobasic sodium phosphate (0.55 mg), polysorbate 80 (0.22 mg) (vegetable origin), trehalose (86 mg), and Water for Injection, USP. The pH is 7.

12 CLINICAL PHARMACOLOGY

12.1 Mechanism of Action

Eculizumab-aagh, the active ingredient in EPYSQLI, is a monoclonal antibody that specifically binds to the complement protein C5 with high affinity, thereby inhibiting its cleavage to C5a and C5b and preventing the generation of the terminal complement complex C5b-9.

Eculizumab products inhibit terminal complement-mediated intravascular hemolysis in PNH patients and complement-mediated thrombotic microangiopathy (TMA) in patients with aHUS.

The precise mechanism by which eculizumab exerts its therapeutic effect in gMG patients is unknown, but is presumed to involve reduction of terminal complement complex C5b-9 deposition at the neuromuscular junction.

12.2 Pharmacodynamics

In the placebo-controlled clinical study (PNH Study 1), eculizumab when administered as recommended reduced serum LDH levels from 2200 ± 1034 U/L (mean ± SD) at baseline to 700 ± 388 U/L by week one and maintained the effect through the end of the study at week 26 (327 ± 433 U/L) in patients with PNH. In the single arm clinical study (PNH Study 2), the effect was maintained through week 52 [see Clinical Studies (14)].

In patients with PNH, aHUS, and gMG, free C5 concentrations of < 0.5 mcg/mL was correlated with complete blockade of terminal complement activity.

12.3 Pharmacokinetics

Following intravenous maintenance doses of 900 mg once every 2 weeks in patients with PNH, the week 26 observed mean ± SD serum eculizumab maximum concentration (Cmax) was 194 ± 76 mcg/mL and the trough concentration (Ctrough) was 97 ± 60 mcg/mL. Following intravenous maintenance doses of 1,200 mg once every 2 weeks in patients with aHUS, the week 26 observed mean ± SD Ctrough was 242 ± 101 mcg/mL. Following intravenous maintenance doses of 1,200 mg once every 2 weeks in adult patients with gMG, the week 26 observed mean ± SD Cmax was 783 ± 288 mcg/mL and the Ctrough was 341 ± 172 mcg/mL.

Steady state was achieved 4 weeks after starting eculizumab treatment, with accumulation ratio of approximately 2-fold in all studied indications. Population pharmacokinetic analyses showed that eculizumab pharmacokinetics were dose-linear and time-independent over the 600 mg to 1,200 mg dose range, with inter-individual variability of 21% to 38%.

Distribution

The eculizumab volume of distribution for a typical 70 kg patient was 5 L to 8 L.

Elimination

The half-life of eculizumab ranged between 141 h to 882 h.

Plasma exchange or infusion increased the clearance of eculizumab by approximately 6.01-fold and reduced the half-life to 90.2 h. Supplemental dosing is recommended when EPYSQLI is administered to patients receiving plasma exchange or infusion [see Dosage and Administration (2.5)].

Specific Populations

Age, Sex, and Race:

The pharmacokinetics of eculizumab were not affected by age (2 months to 85 years), sex, or race.

Renal Impairment:

Renal function did not affect the pharmacokinetics of eculizumab in PNH (creatinine clearance of 8 mL/min to 396 mL/min calculated using Cockcroft-Gault formula), aHUS (estimated glomerular filtration rate [eGFR] of 5 mL/min/1.73 m^2 to105 mL/min/1.73 m^2 using the Modification of Diet in Renal Disease [MDRD] formula), or gMG patients (eGFR of 44 mL/min/1.73 m^2 to 168 mL/min/1.73 m^2 using MDRD formula).

12.6 Immunogenicity

The observed incidence of anti-drug antibodies is highly dependent on the sensitivity and specificity of the assay. Differences in assay methods preclude meaningful comparisons of the incidence of anti-drug antibodies in the studies described below with the incidence of anti-drug antibodies in other studies, including those of eculizumab or of other eculizumab products.

The immunogenicity of eculizumab has been evaluated using two different immunoassays for the detection of anti-eculizumab antibodies: a direct enzyme-linked immunosorbent assay (ELISA) using the Fab fragment of eculizumab as target was used for the PNH indication; and an electro-chemiluminescence (ECL) bridging assay using the eculizumab whole molecule as target was used for the aHUS and gMG indications, as well as for additional patients with PNH. In the PNH population, antibodies to eculizumab were detected in 3/196 (2%) patients using the ELISA assay and in 5/161 (3%) patients using the ECL assay during the entire treatment period. In the aHUS population, antibodies to eculizumab were detected in 3/100 (3%) patients using the ECL assay during the entire treatment period. In the gMG population, none of the 62 adult patients had antibodies to eculizumab detected following the 26-week active treatment.

An ECL based neutralizing assay with a low sensitivity of 2 mcg/mL was performed to detect neutralizing antibodies for the 5 patients with PNH and the 3 patients with aHUS with anti-eculizumab antibody positive samples using the ECL assay. Two of 161 patients with PNH (1.2%) and 1 of 100 patients with aHUS (1%) had low positive values for neutralizing antibodies.

No apparent correlation of antibody development to clinical response was observed.

13 NONCLINICAL TOXICOLOGY

13.1 Carcinogenesis, Mutagenesis, Impairment of Fertility

Long-term animal carcinogenicity studies of eculizumab products have not been conducted.

Genotoxicity studies have not been conducted with eculizumab products.

Effects of eculizumab products upon fertility have not been studied in animals. Intravenous injections of male and female mice with a murine anti-C5 antibody at up to 4-8 times the equivalent of the clinical dose of eculizumab had no adverse effects on mating or fertility.

14 CLINICAL STUDIES

14.1 Paroxysmal Nocturnal Hemoglobinuria (PNH)

The safety and efficacy of eculizumab in PNH patients with hemolysis were assessed in a randomized, double-blind, placebo-controlled 26 week study (PNH Study 1, NCT00122330); PNH patients were also treated with eculizumab in a single arm 52 week study (PNH Study 2, NCT00122304) and in a long- term extension study (E05-001, NCT00122317). Patients received meningococcal vaccination prior to receipt of eculizumab. In all studies, the dose of eculizumab was 600 mg study drug every 7 ± 2 days for 4 weeks, followed by 900 mg 7 ± 2 days later, then 900 mg every 14 ± 2 days for the study duration. Eculizumab was administered as an intravenous infusion over 25 - 45 minutes.

PNH Study 1:

PNH patients with at least four transfusions in the prior 12 months, flow cytometric confirmation of at least 10% PNH cells and platelet counts of at least 100,000/microliter were randomized to either eculizumab (n = 43) or placebo (n = 44). Prior to randomization, all patients underwent an initial observation period to confirm the need for RBC transfusion and to identify the hemoglobin concentration (the "set-point") which would define each patient's hemoglobin stabilization and transfusion outcomes. The hemoglobin set-point was less than or equal to 9 g/dL in patients with symptoms and was less than or equal to 7 g/dL in patients without symptoms. Endpoints related to hemolysis included the numbers of patients achieving hemoglobin stabilization, the number of RBC units transfused, fatigue, and health-related quality of life. To achieve a designation of hemoglobin stabilization, a patient had to maintain a hemoglobin concentration above the hemoglobin set-point and avoid any RBC transfusion for the entire 26 week period. Hemolysis was monitored mainly by the measurement of serum LDH levels, and the proportion of PNH RBCs was monitored by flow cytometry. Patients receiving anticoagulants and systemic corticosteroids at baseline continued these medications. Major baseline characteristics were balanced (see Table 10).

Table 10: PNH Study 1 Patient Baseline Characteristics
 | Study 1
Parameter | Placebo (N=44) | Eculizumab (N=43)
Mean age (SD) | 38 (13) | 42 (16)
Gender - female (%) | 29 (66) | 23 (54)
History of aplastic anemia or myelodysplastic syndrome (%) | 12 (27) | 8 (19)
Patients with history of thrombosis (events) | 8 (11) | 9 (16)
Concomitant anticoagulants (%) | 20 (46) | 24 (56)
Concomitant steroids/immunosuppressant treatments (%) | 16 (36) | 14 (33)
Packed RBC units transfused per patient in previous 12 months (median (Q1,Q3)) | 17 (14, 25) | 18 (12, 24)
Mean Hgb level (g/dL) at setpoint (SD) | 8 (1) | 8 (1)
Pre-treatment LDH levels (median, U/L) | 2,234 | 2,032
Free hemoglobin at baseline (median, mg/dL) | 46 | 41

Patients treated with eculizumab had significantly reduced (p< 0.001) hemolysis resulting in improvements in anemia as indicated by increased hemoglobin stabilization and reduced need for RBC transfusions compared to placebo treated patients (see Table 11). These effects were seen among patients within each of the three pre-study RBC transfusion strata (4 - 14 units; 15 - 25 units; > 25 units). After 3 weeks of eculizumab treatment, patients reported less fatigue and improved health- related quality of life. Because of the study sample size and duration, the effects of eculizumab products on thrombotic events could not be determined.

Table 11: PNH Study 1 Results
 | Placebo (N=44) | Eculizumab (N=43)
Percentage of patients with stabilized hemoglobin levels | 0 | 49
Packed RBC units transfused per patient (median) | 10 | 0
(range) | (2 - 21) | (0 - 16)
Transfusion avoidance (%) | 0 | 51
LDH levels at end of study (median, U/L) | 2,167 | 239
Free hemoglobin at end of study (median, mg/dL) | 62 | 5

PNH Study 2 and Extension Study:

PNH patients with at least one transfusion in the prior 24 months and at least 30,000 platelets/microliter received eculizumab over a 52-week period. Concomitant medications included anti- thrombotic agents in 63% of the patients and systemic corticosteroids in 40% of the patients. Overall, 96 of the 97 enrolled patients completed the study (one patient died following a thrombotic event). A reduction in intravascular hemolysis as measured by serum LDH levels was sustained for the treatment period and resulted in a reduced need for RBC transfusion and less fatigue. 187 eculizumab- treated PNH patients were enrolled in a long term extension study. All patients sustained a reduction in intravascular hemolysis over a total eculizumab exposure time ranging from 10 to 54 months. There were fewer thrombotic events with eculizumab treatment than during the same period of time prior to treatment. However, the majority of patients received concomitant anticoagulants; the effects of anticoagulant withdrawal during eculizumab products therapy was not studied [see Warnings and Precautions (5.5)].

14.2 Atypical Hemolytic Uremic Syndrome (aHUS)

Five single-arm studies [four prospective: C08-002A/B (NCT00844545 and NCT00844844), C08- 003A/B (NCT00838513 and NCT00844428), C10-003 (NCT01193348), and C10-004 (NCT01194973); and one retrospective: C09-001r (NCT01770951)] evaluated the safety and efficacy of eculizumab for the treatment of aHUS. Patients with aHUS received meningococcal vaccination prior to receipt of eculizumab or received prophylactic treatment with antibiotics until 2 weeks after vaccination. In all studies, the dose of eculizumab in adult and adolescent patients was 900 mg every 7 ± 2 days for 4 weeks, followed by 1,200 mg 7 ± 2 days later, then 1,200 mg every 14 ± 2 days thereafter. The dosage regimen for pediatric patients weighing less than 40 kg enrolled in Study C09-001r and Study C10-003 was based on body weight [see Dosage and Administration (2.3)]. Efficacy evaluations were based on thrombotic microangiopathy (TMA) endpoints.

Endpoints related to TMA included the following:

- platelet count change from baseline
- hematologic normalization (maintenance of normal platelet counts and LDH levels for at least four weeks)
- complete TMA response (hematologic normalization plus at least a 25% reduction in serum creatinine for a minimum of four weeks)
- TMA-event free status (absence for at least 12 weeks of a decrease in platelet count of >25% from baseline, plasma exchange or plasma infusion, and new dialysis requirement)
- Daily TMA intervention rate (defined as the number of plasma exchange or plasma infusion interventions and the number of new dialyses required per patient per day).

aHUS Resistant to PE/PI (Study C08-002A/B)

Study C08-002A/B enrolled patients who displayed signs of thrombotic microangiopathy (TMA) despite receiving at least four PE/PI treatments the week prior to screening. One patient had no PE/PI the week prior to screening because of PE/PI intolerance. In order to qualify for enrollment, patients were required to have a platelet count ≤150 x 10^9/L, evidence of hemolysis such as an elevation in serum LDH, and serum creatinine above the upper limits of normal, without the need for chronic dialysis. The median patient age was 28 (range: 17 to 68 years). Patients enrolled in Study C08- 002A/B were required to have ADAMTS13 activity level above 5%; observed range of values in the trial were 70%-121%. Seventy-six percent of patients had an identified complement regulatory factor mutation or auto-antibody. Table 12 summarizes the key baseline clinical and disease-related characteristics of patients enrolled in Study C08-002A/B.

Table 12: Baseline Characteristics of Patients Enrolled in Study C08-002A/B
Parameter | C08-002A/B (N=17)
Time from aHUS diagnosis until screening in months, median (min, max) | 10 (0.26, 236)
Time from current clinical TMA manifestation until screening in months, median (min, max) | <1 (<1, 4)
Baseline platelet count (× 10^9/L), median (range) | 118 (62, 161)
Baseline LDH (U/L), median (range) | 269 (134, 634)

Patients in Study C08-002A/B received eculizumab for a minimum of 26 weeks. In Study C08-002A/B, the median duration of eculizumab therapy was approximately 100 weeks (range: 2 weeks to 145 weeks).

Renal function, as measured by eGFR, was improved and maintained during eculizumab therapy. The mean eGFR (± SD) increased from 23 ± 15 mL/min/1.73m^2 at baseline to 56 ± 40 mL/min/1.73m^2 by 26 weeks; this effect was maintained through 2 years (56 ± 30 mL/min/1.73m^2). Four of the five patients who required dialysis at baseline were able to discontinue dialysis.

Reduction in terminal complement activity and an increase in platelet count relative to baseline were observed after commencement of eculizumab. Eculizumab reduced signs of complement-mediated TMA activity, as shown by an increase in mean platelet counts from baseline to 26 weeks. In Study C08- 002A/B, mean platelet count (± SD) increased from 109 ± 32 x10^9/L at baseline to 169 ± 72 x10^9/L by one week; this effect was maintained through 26 weeks (210 ± 68 x10^9/L), and 2 years (205 ± 46 x10^9/L). When treatment was continued for more than 26 weeks, two additional patients achieved Hematologic Normalization as well as Complete TMA response. Hematologic Normalization and Complete TMA response were maintained by all responders. In Study C08-002A/B, responses to eculizumab were similar in patients with and without identified mutations in genes encoding complement regulatory factor proteins.

Table 13 summarizes the efficacy results for Study C08-002A/B.

Table 13: Efficacy Results for Study C08-002A/B
Efficacy Parameter | Study C08-002A/B at 26 wks^1 (N=17) | Study C08-002A/B at 2 yrs^2 (N=17)
Complete TMA response, n (%) Median Duration of complete TMA response, weeks (range) | 11 (65) 38 (25, 56) | 13 (77) 99 (25, 139)
eGFR improvement ≥15 mL/min/1.73 m^2, n (%) Median duration of eGFR improvement, days (range) | 9 (53) 251 (70, 392) | 10 (59) ND
Hematologic normalization, n (%) Median Duration of hematologic normalization, weeks (range) | 13 (76) 37 (25, 62) | 15 (88) 99 (25, 145)
TMA event-free status, n (%) | 15 (88) | 15 (88)
Daily TMA intervention rate, median (range) Before eculizumab On eculizumab treatment | 0.82 (0.04, 1.52) 0 (0, 0.31) | 0.82 (0.04, 1.52) 0 (0, 0.36)
^1.At data cut-off (September 8, 2010).
^2.At data cut-off (April 20, 2012).

aHUS Sensitive to PE/PI (Study C08-003A/B)

Study C08-003A/B enrolled patients undergoing chronic PE/PI who generally did not display hematologic signs of ongoing thrombotic microangiopathy (TMA). All patients had received PT at least once every two weeks, but no more than three times per week, for a minimum of eight weeks prior to the first eculizumab dose. Patients on chronic dialysis were permitted to enroll in Study C08- 003A/B. The median patient age was 28 years (range: 13 to 63 years). Patients enrolled in Study C08- 003A/B were required to have ADAMTS13 activity level above 5%; observed range of values in the trial were 37%-118%. Seventy percent of patients had an identified complement regulatory factor mutation or auto-antibody. Table 14 summarizes the key baseline clinical and disease-related characteristics of patients enrolled in Study C08-003A/B.

Table 14: Baseline Characteristics of Patients Enrolled in Study C08-003A/B
Parameter | Study C08-003A/B (N=20)
Time from aHUS diagnosis until screening in months, median (min, max) | 48 (0.66, 286)
Time from current clinical TMA manifestation until screening in months, median (min, max) | 9 (1, 45)
Baseline platelet count (× 10^9/L), median (range) | 218 (105, 421)
Baseline LDH (U/L), median (range) | 200 (151, 391)

Patients in Study C08-003A/B received eculizumab for a minimum of 26 weeks. In Study C08-003A/B, the median duration of eculizumab therapy was approximately 114 weeks (range: 26 to 129 weeks).

Renal function, as measured by eGFR, was maintained during eculizumab therapy. The mean eGFR (± SD) was 31 ± 19 mL/min/1.73m^2 at baseline, and was maintained through 26 weeks (37 ± 21 mL/min/1.73m^2) and 2 years (40 ± 18 mL/min/1.73m^2). No patient required new dialysis with eculizumab.

Reduction in terminal complement activity was observed in all patients after the commencement of eculizumab. Eculizumab reduced signs of complement-mediated TMA activity, as shown by an increase in mean platelet counts from baseline to 26 weeks. Platelet counts were maintained at normal levels despite the elimination of PE/PI. The mean platelet count (± SD) was 228 ± 78 x 10^9/L at baseline, 233 ± 69 x 10^9/L at week 26, and 224 ± 52 x 10^9/L at 2 years. When treatment was continued for more than 26 weeks, six additional patients achieved Complete TMA response. Complete TMA Response and Hematologic Normalization were maintained by all responders. In Study C08-003A/B, responses to eculizumab were similar in patients with and without identified mutations in genes encoding complement regulatory factor proteins.

Table 15 summarizes the efficacy results for Study C08-003A/B.

Table 15: Efficacy Results for Study C08-003A/B
Efficacy Parameter | Study C08-003A/B at 26 wks^1 (N=20) | Study C08-003A/B at 2 yrs^2 (N=20)
Complete TMA response, n (%) Median duration of complete TMA response, weeks (range) | 5 (25) 32 (12, 38) | 11 (55) 68 (38, 109)
eGFR improvement ≥15 mL/min/1.73 m^2, n (%) | 1 (5) | 8 (40)
TMA Event-free status n (%) | 16 (80) | 19 (95)
Daily TMA intervention rate, median (range) Before eculizumab On eculizumab treatment | 0.23 (0.05, 1.07) 0 | 0.23 (0.05, 1.07) 0 (0, 0.01)
Hematologic normalization^4, n (%) Median duration of hematologic normalization, weeks (range)^3 | 18 (90) 38 (22, 52) | 18 (90) 114 (33, 125)
^1. At data cut-off (September 8, 2010).
^2. At data cut-off (April 20, 2012).
^3. Calculated at each post-dose day of measurement (excluding Days 1 to 4) using a repeated measurement ANOVA model.
^4. In Study C08-003A/B, 85% of patients had normal platelet counts and 80% of patients had normal serum LDH levels at baseline, so hematologic normalization in this population reflects maintenance of normal parameters in the absence of PE/PI.

Retrospective Study in Patients with aHUS (C09-001r)

The efficacy results for the aHUS retrospective study (Study C09-001r) were generally consistent with results of the two prospective studies. Eculizumab reduced signs of complement-mediated TMA activity, as shown by an increase in mean platelet counts from baseline. Mean platelet count (± SD) increased from 171 ± 83 x10^9/L at baseline to 233 ±109 x10^9/L after one week of therapy; this effect was maintained through 26 weeks (mean platelet count (± SD) at week 26: 254 ± 79 x10^9/L).

A total of 19 pediatric patients (ages 2 months to 17 years) received eculizumab in Study C09-001r. The median duration of eculizumab therapy was 16 weeks (range 4 to 70 weeks) for children <2 years of age (n=5), 31 weeks (range 19 to 63 weeks) for children 2 to <12 years of age (n=10), and 38 weeks (range 1 to 69 weeks) for patients 12 to <18 years of age (n=4). Fifty-three percent of pediatric patients had an identified complement regulatory factor mutation or auto-antibody.

Overall, the efficacy results for these pediatric patients appeared consistent with what was observed in patients enrolled in Studies C08-002A/B and C08-003A/B (Table 16). No pediatric patient required new dialysis during treatment with eculizumab.

Table 16: Efficacy Results in Pediatric Patients Enrolled in Study C09-001r
Efficacy Parameter | <2 yrs (N=5) | 2 to <12 yrs (N=10) | 12 to <18 yrs (N=4) | Total (N=19)
Complete TMA response, n (%) | 2 (40) | 5 (50) | 1 (25) | 8 (42)
Patients with eGFR improvement ≥ 15 mL/min/1.73 m^2, n (%)^2 | 2 (40) | 6 (60) | 1 (25) | 9 (47)
Platelet count normalization, n (%)^1 | 4 (80) | 10 (100) | 3 (75) | 17 (89)
Hematologic Normalization, n (%) | 2 (40) | 5 (50) | 1 (25) | 8 (42)
Daily TMA intervention rate, median (range) Before eculizumab On eculizumab treatment | 1 (0, 2) <1 (0, <1) | <1 (0.07, 1.46) 0 (0, <1) | <1 (0, 1) 0 (0, <1) | 0.31 (0.00, 2.38) 0.00 (0.00 , 0.08)
^1. Platelet count normalization was defined as a platelet count of at least 150,000 X 10^9/L on at least two consecutive measurements spanning a period of at least 4 weeks.
^2. Of the 9 patients who experienced an eGFR improvement of at least 15 mL/min/1.73 m^2, one received dialysis throughout the study period and another received eculizumab as prophylaxis following renal allograft transplantation.

Adult Patients with aHUS (Study C10-004)

Study C10-004 enrolled patients who displayed signs of thrombotic microangiopathy (TMA). In order to qualify for enrollment, patients were required to have a platelet count < lower limit of normal range (LLN), evidence of hemolysis such as an elevation in serum LDH, and serum creatinine above the upper limits of normal, without the need for chronic dialysis. The median patient age was 35 (range: 18 to 80 years). All patients enrolled in Study C10-004 were required to have ADAMTS13 activity level above 5%; observed range of values in the trial were 28%-116%. Fifty-one percent of patients had an identified complement regulatory factor mutation or auto-antibody. A total of 35 patients received PE/PI prior to eculizumab. Table 17 summarizes the key baseline clinical and disease-related characteristics of patients enrolled in Study C10-004.

Table 17: Baseline Characteristics of Patients Enrolled in Study C10-004
Parameter | Study C10-004 (N=41)
Time from aHUS diagnosis until start of study drug in months, median (range) | 0.79 (0.03 – 311)
Time from current clinical TMA manifestation until first study dose in months, median (range) | 0.52 (0.03-19)
Baseline platelet count (× 10^9/L), median (range) | 125 (16 – 332)
Baseline LDH (U/L), median (range) | 375 (131 – 3318)

Patients in Study C10-004 received eculizumab for a minimum of 26 weeks. In Study C10-004, the median duration of eculizumab therapy was approximately 50 weeks (range: 13 weeks to 86 weeks).

Renal function, as measured by eGFR, was improved during eculizumab therapy. The mean eGFR (± SD) increased from 17 ± 12 mL/min/1.73m^2 at baseline to 47 ± 24 mL/min/1.73m^2 by 26 weeks. Twenty of the 24 patients who required dialysis at study baseline were able to discontinue dialysis during eculizumab treatment.

Reduction in terminal complement activity and an increase in platelet count relative to baseline were observed after commencement of eculizumab. Eculizumab reduced signs of complement-mediated TMA activity, as shown by an increase in mean platelet counts from baseline to 26 weeks. In Study C10- 004, mean platelet count (± SD) increased from 119 ± 66 x10^9/L at baseline to 200 ± 84 x10^9/L by one week; this effect was maintained through 26 weeks (mean platelet count (± SD) at week 26: 252 ± 70 x10^9/L). In Study C10-004, responses to eculizumab were similar in patients with and without identified mutations in genes encoding complement regulatory factor proteins or auto-antibodies to factor H.

Table 18 summarizes the efficacy results for Study C10-004.

Table 18: Efficacy Results for Study C10-004
Efficacy Parameter | Study C10-004 (N=41)
Complete TMA response, n (%), 95% CI Median duration of complete TMA response, weeks (range) | 23 (56) 40,72 42 (6, 75)
Patients with eGFR improvement ≥ 15 mL/min/1.73m^2, n (%) | 22 (54)
Hematologic Normalization, n (%) Median duration of hematologic normalization, weeks (range) | 36 (88) 46 (10, 75)
TMA Event-free Status, n (%) | 37 (90)
Daily TMA Intervention Rate, median (range) Before eculizumab On eculizumab treatment | 0.63 (0, 1.38) 0 (0, 0.58)

Pediatric and Adolescent Patients with aHUS (Study C10-003)

Study C10-003 enrolled patients who were required to have a platelet count < lower limit of normal range (LLN), evidence of hemolysis such as an elevation in serum LDH above the upper limits of normal, serum creatinine level ≥97 percentile for age without the need for chronic dialysis. The median patient age was 6.5 (range: 5 months to 17 years). Patients enrolled in Study C10-003 were required to have ADAMTS13 activity level above 5%; observed range of values in the trial were 38%-121%. Fifty percent of patients had an identified complement regulatory factor mutation or auto-antibody. A total of 10 patients received PE/PI prior to eculizumab. Table 19 summarizes the key baseline clinical and disease-related characteristics of patients enrolled in Study C10-003.

Table 19: Baseline Characteristics of Patients Enrolled in Study C10-003
Parameter | Patients 1 month to <12 years (N=18) | All Patients (N=22)
Time from aHUS diagnosis until start of study drug in months, median (range) | 0.51 (0.03 – 58) | 0.56 (0.03-191)
Time from current clinical TMA manifestation until first study dose in months, median (range) | 0.23 (0.03 – 4) | 0.2 (0.03-4)
Baseline platelet count (x 10^9/L), median (range) | 110 (19-146) | 91 (19-146)
Baseline LDH (U/L) median (range) | 1510 (282-7164) | 1244 (282-7164)

Patients in Study C10-003 received eculizumab for a minimum of 26 weeks. In Study C10-003, the median duration of eculizumab therapy was approximately 44 weeks (range: 1 dose to 88 weeks).

Renal function, as measured by eGFR, was improved during eculizumab therapy. The mean eGFR (± SD) increased from 33 ± 30 mL/min/1.73m^2 at baseline to 98 ± 44 mL/min/1.73m^2 by 26 weeks. Among the 20 patients with a CKD stage ≥2 at baseline, 17 (85%) achieved a CKD improvement of ≥1 stage. Among the 16 patients ages 1 month to <12 years with a CKD stage ≥2 at baseline, 14 (88%) achieved a CKD improvement by ≥1 stage. Nine of the 11 patients who required dialysis at study baseline were able to discontinue dialysis during eculizumab treatment. Responses were observed across all ages from 5 months to 17 years of age.

Reduction in terminal complement activity was observed in all patients after commencement of eculizumab. Eculizumab reduced signs of complement-mediated TMA activity, as shown by an increase in mean platelet counts from baseline to 26 weeks. The mean platelet count (± SD) increased from 88 ± 42 x10^9/L at baseline to 281 ± 123 x10^9/L by one week; this effect was maintained through 26 weeks (mean platelet count (±SD) at week 26: 293 ± 106 x10^9/L). In Study C10-003, responses to eculizumab were similar in patients with and without identified mutations in genes encoding complement regulatory factor proteins or auto-antibodies to factor H.

Table 20 summarizes the efficacy results for Study C10-003.

Table 20: Efficacy Results for Study C10-003
Efficacy Parameter | Patients 1 month to <12 years (N=18) | All Patients (N=22)
Complete TMA response, n (%) 95% CI Median Duration of complete TMA response, weeks (range)^1 | 11 (61) 36, 83 40 (14, 77) | 14 (64) 41, 83 37 (14, 77)
eGFR improvement ≥15 mL/min/ 1.73 m^2•n (%) | 16 (89) | 19 (86)
Complete Hematologic Normalization, n (%) Median Duration of complete hematologic normalization, weeks (range) | 14 (78) 38 (14, 77) | 18 (82) 38 (14, 77)
TMA Event-Free Status, n (%) | 17 (94) | 21 (95)
Daily TMA Intervention rate, median (range) Before eculizumab treatment On eculizumab treatment | 0.2 (0, 1.7) 0 (0, 0.01) | 0.4 (0, 1.7) 0 (0, 0.01)
^1. Through data cutoff (October 12, 2012).

14.3 Generalized Myasthenia Gravis (gMG)

The efficacy of eculizumab for the treatment of gMG was established in Study ECU-MG-301 (NCT01997229), a 26-week randomized, double-blind, parallel-group, placebo-controlled, multi-center trial that enrolled adult patients who met the following criteria at screening:

1. Positive serologic test for anti-AChR antibodies,
2. Myasthenia Gravis Foundation of America (MGFA) Clinical Classification Class II to IV,
3. MG-Activities of Daily Living (MG-ADL) total score ≥6,
4. Failed treatment over 1 year or more with 2 or more immunosuppressive therapies (ISTs) either in combination or as monotherapy, or failed at least 1 IST and required chronic plasmapheresis or plasma exchange (PE) or intravenous immunoglobulin (IVIg).

A total of 62 patients were randomized to receive eculizumab treatment and 63 were randomized to receive placebo. Baseline characteristics were similar between treatment groups, including age at diagnosis (38 years in each group), gender [66% female (eculizumab) versus 65% female (placebo)], and duration of gMG [9.9 (eculizumab) versus 9.2 (placebo) years]. Over 95% of patients in each group were receiving acetylcholinesterase (AchE) inhibitors, and 98% were receiving immunosuppressant therapies (ISTs). Approximately 50% of each group had been previously treated with at least 3 ISTs.

Eculizumab was administered according to the recommended dosage regimen [see Dosage and Administration (2.4)].

The primary efficacy endpoint for Study ECU-MG-301 was a comparison of the change from baseline between treatment groups in the Myasthenia Gravis-Specific Activities of Daily Living scale (MGADL) total score at Week 26. The MG-ADL is a categorical scale that assesses the impact on daily function of 8 signs or symptoms that are typically affected in gMG. Each item is assessed on a 4point scale where a score of 0 represents normal function and a score of 3 represents loss of ability to perform that function (total score 0-24). A statistically significant difference favoring eculizumab was observed in the mean change from baseline to Week 26 in MG-ADL total scores [-4.2 points in the eculizumab-treated group compared with -2.3 points in the placebo-treated group (p=0.006)].

A key secondary endpoint in Study ECU-MG-301 was the change from baseline in the Quantitative Myasthenia Gravis (QMG) total score at Week 26. The QMG is a 13-item categorical scale assessing muscle weakness. Each item is assessed on a 4-point scale where a score of 0 represents no weakness and a score of 3 represents severe weakness (total score 0-39). A statistically significant difference favoring eculizumab was observed in the mean change from baseline to Week 26 in QMG total scores [-4.6 points in the eculizumab-treated group compared with -1.6 points in the placebo-treated group (p=0.001)].

The results of the analysis of the MG-ADL and QMG from Study ECU-MG-301 are shown in Table 21.

Table 21: Analysis of Change from Baseline to Week 26 in MG-ADL and QMG Total Scores in Study ECU-MG-301
Efficacy Endpoints | Eculizumab-LS Mean (N=62) (SEM) | Placebo-LS Mean (N=63) (SEM) | Eculizumab change relative to placebo – LS Mean Difference (95% CI) | p-values
MG-ADL | -4.2 (0.49) | -2.3 (0.48) | -1.9 (-3.3, -0.6) | (0.006a; 0.014b)
QMG | -4.6 (0.60) | -1.6 (0.59) | -3.0 (-4.6, -1.3) | (0.001a; 0.005b)
SEM= Standard Error of the Mean; eculizumab-LSMean = least square mean for the treatment group; Placebo-LSMean = least square mean for the placebo group; LSMean-Difference (95% CI) = Difference in least square mean with 95% confidence interval; p-values (testing the null hypothesis that there is no difference between the two treatment arms
a: in least square means at Week 26 using a repeated measure analysis; b: in ranks at Week 26 using a worst rank analysis).

In Study ECU-MG-301 , a clinical response was defined in the MG-ADL total score as at least a 3-point improvement and in QMG total score as at least a 5-point improvement. The proportion of clinical responders at Week 26 with no rescue therapy was statistically significantly higher for eculizumab compared to placebo for both measures. For both endpoints, and also at higher response thresholds (≥4-, 5-, 6-, 7-, or 8-point improvement on MG-ADL, and ≥6-, 7-, 8-, 9-, or 10-point improvement on QMG), the proportion of clinical responders was consistently greater for eculizumab compared to placebo. Available data suggest that clinical response is usually achieved by 12 weeks of eculizumab treatment.

16 HOW SUPPLIED/STORAGE AND HANDLING

EPYSQLI (eculizumab-aagh) injection is a sterile, preservative-free, clear to slightly opalescent and colorless solution supplied as one 300 mg/30 mL (10 mg/mL) single-dose vial per carton (NDC 51759-208-13).

- Store EPYSQLI vials in a refrigerator at 2°C to 8°C (36°F to 46°F) in the original carton to protect from light until time of use. DO NOT FREEZE. DO NOT SHAKE.
- Prior to administration, if needed, unopened vials of EPYSQLI may be stored in the original carton at controlled room temperature [not more than 30°C (86°F)] for a single 1 month period and then returned to refrigeration for 3 days.
- Do not use beyond the expiration date shown on the carton.

Refer to Dosage and Administration (2) for information on the stability and storage of diluted solutions of EPYSQLI.

17 PATIENT COUNSELING INFORMATION

Advise the patients and/or caregivers to read the FDA-approved patient labeling (Medication Guide).

Serious Meningococcal Infections

Advise patients of the risk of serious meningococcal infection. Inform patients of the need to complete or update their meningococcal vaccinations at least 2 weeks prior to receiving the first dose of EPYSQLI or receive antibacterial drug prophylaxis if EPYSQLI treatment must be initiated immediately and they have not been previously vaccinated. Inform patients of the requirement to be revaccinated according to current ACIP recommendations for meningococcal infection while on EPYSQLI therapy [see Warnings and Precautions (5.1)].

Inform patients that vaccination may not prevent serious meningococcal infection and to seek immediate medical attention if the following signs or symptoms occur [see Warnings and Precautions (5.1)]:

- fever
- fever and a rash
- fever with high heart rate
- headache with nausea or vomiting
- headache and a fever
- headache with a stiff neck or stiff back
- confusion
- muscle aches with flu-like symptoms
- eyes sensitive to light

Inform patients that they will be given a Patient Safety Card for EPYSQLI that they should carry with them at all times during and for 3 months following treatment with EPYSQLI. This card describes symptoms which, if experienced, should prompt the patient to immediately seek medical evaluation.

EPYSQLI REMS

EPYSQLI is available only through a restricted program called EPYSQLI REMS [see Warnings and Precautions (5.2)].

Inform the patient of the following notable requirements:

- Patients must receive counseling about the risk of serious meningococcal infections.
- Patients must receive written educational materials about this risk.
- Patients must be instructed to carry the Patient Safety Card with them at all times during and for 3 months following treatment with EPYSQLI.
- Patients must be instructed to complete or update meningococcal vaccines for serogroups A, C, W, Y and B per ACIP recommendations as directed by the prescriber prior to treatment with EPYSQLI.
- Patients must receive antibiotics as directed by the prescriber if they are not up to date with meningococcal vaccines and have to start EPYSQLI right away.

Other Infections

Counsel patients about gonorrhea prevention and advise regular testing for patients at-risk.

Inform patients that there may be an increased risk of other types of infections, particularly those due to encapsulated bacteria.

Aspergillus infections have occurred in immunocompromised and neutropenic patients.

Inform parents or caregivers of children receiving EPYSQLI for the treatment of Ahus that their child should be vaccinated against Streptococcus pneumoniae and Haemophilus influenzae type b (Hib) according to current medical guidelines.

Infusion-Related Reactions

Advise patients that administration of EPYSQLI may result in infusion-related reactions.

Discontinuation

Inform patients with PNH that they may develop serious hemolysis due to PNH when EPYSQLI is discontinued and that they will be monitored by their healthcare professional for at least 8 weeks following EPYSQLI discontinuation.

Inform patients with aHUS that there is a potential for TMA complications due to aHUS when EPYSQLI is discontinued and that they will be monitored by their healthcare professional for at least 12 weeks following EPYSQLI discontinuation. Inform patients who discontinue EPYSQLI to keep the Patient Safety Card with them for three months after the last EPYSQLI dose, because the increased risk of meningococcal infection persists for several weeks following discontinuation of EPYSQLI.

Manufactured by:

Samsung Bioepis Co., Ltd.
76, Songdogyoyuk-ro,
Yeonsu-gu, Incheon, 21987
Republic of Korea

US License Number 2046

Product of Australia

Manufactured for:
Teva Pharmaceuticals
Parsippany, NJ 07054

MEDICATION GUIDE
EPYSQLI® (eh-pis'-klee)
(eculizumab-aagh)
injection, for intravenous use

What is the most important information I should know about EPYSQLI?
EPYSQLI is a medicine that affects your immune system. EPYSQLI may lower the ability of your immune system to fight infections.

- EPYSQLI increases your chance of getting serious meningococcal infections caused by Neisseria meningitidisbacteria. Meningococcal infections may quickly become life-threatening or cause death if not recognized and treated early.
  - You must complete or update your meningococcal vaccines at least 2 weeks before your first dose of EPYSQLI.
  - If you have not completed your meningococcal vaccines and EPYSQLI must be started right away, you should receive the required vaccine(s) as soon as possible.
  - If you have not been vaccinated and EPYSQLI must be started right away, you should also receive antibiotics to take for as long as your healthcare provider tells you.
  - If you had a meningococcal vaccine in the past, you might need additional vaccines before starting EPYSQLI. Your healthcare provider will decide if you need additional meningococcal vaccines.
  - Meningococcal vaccines do not prevent all meningococcal infections. Call your healthcare provider or get emergency medical care right away if you get any of these signs and symptoms of a serious meningococcal infection:

- fever
- fever with high heart rate
- headache and fever
- confusion
- muscle aches with flu-like symptoms

- fever and a rash
- headache with nausea or vomiting
- headache with a stiff neck or stiff back
- eyes sensitive to light

Your healthcare provider will give you a Patient Safety Card about the risk of serious meningococcal infection. Carry it with you at all times during treatment and for 3 months after your last dose of EPYSQLI. Your risk of meningococcal infection may continue for several weeks after your last dose of EPYSQLI. It is important to show this card to any healthcare provider who treats you. This will help them diagnose and treat you quickly.
EPYSQLI is only available through a program called the EPYSQLI Risk Evaluation and Mitigation Strategy (REMS). Before you can receive EPYSQLI, your healthcare provider must:

- enroll in the EPYSQLI REMS program
- counsel you about the risk of serious meningococcal infections
- give you information about the signs and symptoms of serious meningococcal infection
- make sure that you are vaccinated against serious infections caused by meningococcal bacteria and that you receive antibiotics if you need to start EPYSQLI right away and you are not up to date on your vaccines
- give you a Patient Safety Card about your risk of meningococcal infection, as discussed above

EPYSQLI may also increase the risk of other types of serious infections caused by encapsulated bacteria, including Streptococcus pneumoniae, Haemophilus influenzae, and Neisseria gonorrhoeae.

- If your child is treated with EPYSQLI, your child should receive vaccines against Streptococcus pneumoniae and Haemophilus influenzae type b (Hib).
- Certain people may be at risk of serious infections with gonorrhea. Talk to your healthcare provider about whether you are at risk for gonorrhea infection, about gonorrhea prevention, and regular testing.
- Certain fungal infections (aspergillus) may also happen if you take EPYSQLI and have a weak immune system or a low white blood cell count.

For more information about side effects, see "What are the possible side effects of EPYSQLI?"

What is EPYSQLI?
EPYSQLI is a prescription medicine used to treat:

- people with paroxysmal nocturnal hemoglobinuria (PNH).
- people with atypical hemolytic uremic syndrome (aHUS).
  EPYSQLI is not for use in treating people with Shiga toxin E. coli related hemolytic uremic syndrome (STEC- HUS).
- adults with generalized myasthenia gravis (gMG) who are anti-acetylcholine receptor (AchR) antibody positive.It is not known if EPYSQLI is safe and effective in children with PNH.

Who should not receive EPYSQLI?
Do not receive EPYSQLI if you have a serious meningococcal infection when you are starting EPYSQLI treatment.

Before you receive EPYSQLI, tell your healthcare provider about all of your medical conditions, including if you:

- have an infection or fever.
- are pregnant or plan to become pregnant. It is not known if EPYSQLI will harm your unborn baby.
- are breastfeeding or plan to breastfeed. It is not known if EPYSQLI passes into your breast milk.

Tell your healthcare provider about all the medicines you take, including prescription and over-the-counter medicines, vitamins, and herbal supplements. EPYSQLI and other medicines can affect each other causing side effects.
Know the medications you take and the vaccines you receive. Keep a list of them to show your healthcare provider and pharmacist when you get a new medicine.

How should I receive EPYSQLI?

- Your healthcare provider will give you EPYSQLI into your vein through an intravenous (IV) line usually over 35 minutes in adults and 1 to 4 hours in children.
- Adults will usually receive an EPYSQLI infusion:
  - weekly for 5 weeks, then
  - every 2 weeks.
- Children less than 18 years of age, your healthcare provider will decide how often you will receive EPYSQLI depending on your age and body weight.
- After each infusion, you should be monitored for at least 1 hour for infusion-related reactions. See "What are the possible side effects of EPYSQLI?" If you have an infusion-related reaction during your EPYSQLI infusion, your healthcare provider may decide to give EPYSQLI more slowly or stop your infusion.
- If you miss an EPYSQLI infusion, call your healthcare provider right away.
- If you have PNH, your healthcare provider will need to monitor you closely for at least 8 weeks after stopping EPYSQLI. Stopping treatment with EPYSQLI may cause breakdown of your red blood cells due to PNH.
  Symptoms or problems that can happen due to red blood cell breakdown include:

- drop in the number of your red blood cell count
- kidney problems

- drop in your platelet
- counts
- blood clots

- confusion
- difficulty breathing
- chest pain

- If you have aHUS, your healthcare provider will need to monitor you closely for at least 12 weeks after stopping EPYSQLI for signs of worsening aHUS symptoms or problems related to abnormal clotting (thrombotic microangiopathy).
  Symptoms or problems that can happen with abnormal clotting may include:

- stroke
- difficulty breathing

- confusion
- kidney problems

- seizure
- swelling in arms or legs

- chest pain (angina)
- a drop in your platelet count

What are the possible side effects of EPYSQLI?
EPYSQLI can cause serious side effects including:

- See "What is the most important information I should know about EPYSQLI?"
- Serious infusion-related reactions. Serious infusion-related reactions can happen during your EPYSQLI infusion. Tell your healthcare provider or nurse right away if you get any of these symptoms during your EPYSQLI infusion:
  - chest pain
  - trouble breathing or shortness of breath
  - swelling of your face, tongue, or throat
  - feel faint or pass out

If you have an infusion-related reaction to EPYSQLI, your healthcare provider may need to infuse EPYSQLI more slowly, or stop EPYSQLI. See "How should I receive EPYSQLI?"
The most common side effects in people with PNH treated with EPYSQLI include:

- headache
- pain or swelling of your nose or throat (nasopharyngitis)

- back pain
- nausea

The most common side effects in people with aHUS treated with EPYSQLI include:

- headache
- diarrhea
- high blood pressure (hypertension)
- common cold (upper respiratory infection)

- stomach-area(abdominal) pain
- vomiting
- pain or swelling of
- your nose or throat (nasopharyngitis)

- low red blood cell (anemia)
- cough
- swelling of legs or
- feet (peripheral edema)

- nausea
- urinary tract infections
- fever

The most common side effects in people with gMG treated with EPYSQLI include:

- muscle and joint (musculoskeletal) pain

Tell your healthcare provider about any side effect that bothers you or that does not go away. These are not all the possible side effects of EPYSQLI.
Call your doctor for medical advice about side effects. You may report side effects to FDA at 1-800-FDA-1088.

General information about the safe and effective use of EPYSQLI.
Medicines are sometimes prescribed for purposes other than those listed in a Medication Guide. You can ask your pharmacist or healthcare provider for information about EPYSQLI that is written for health professionals.

What are the ingredients in EPYSQLI?
Active ingredient: eculizumab-aagh
Inactive ingredients: dibasic sodium phosphate, monobasic sodium phosphate, polysorbate 80 (vegetable origin), trehalose, and Water for Injection.
Manufactured by Samsung Bioepis Co., Ltd.,
76, Songdogyoyuk-ro, Yeonsu-gu, Incheon 21987 Republic of Korea.
US License Number 2046
Manufactured for Teva Pharmaceuticals
Parsippany, NJ 07054

This Medication Guide has been approved by the U.S. Food and Drug Administration.

Revised: 11/2025

PRINCIPAL DISPLAY PANEL - 30 mL Vial Label

NDC 51759-208-13

Epysqli®
(eculizumab-aagh)
Injection
300 mg/30 mL
(10 mg/mL)

For Intravenous Infusion
Must dilute before use.
30 mL Single-Dose Vial
Discard Unused Portion

000303748-01

PRINCIPAL DISPLAY PANEL - 30 mL Vial Carton

NDC 51759-208-13

Epysqli®
(eculizumab-aagh)
Injection
300 mg/30 mL
(10 mg/mL)

For Intravenous Infusion

Must dilute before use.

ATTENTION PHARMACIST:
Each patient is required to
receive the enclosed
Medication Guide.

One 30 mL Single-Dose Vial.

Discard Unused Portion.

SAMSUNG
BIOEPIS | teva